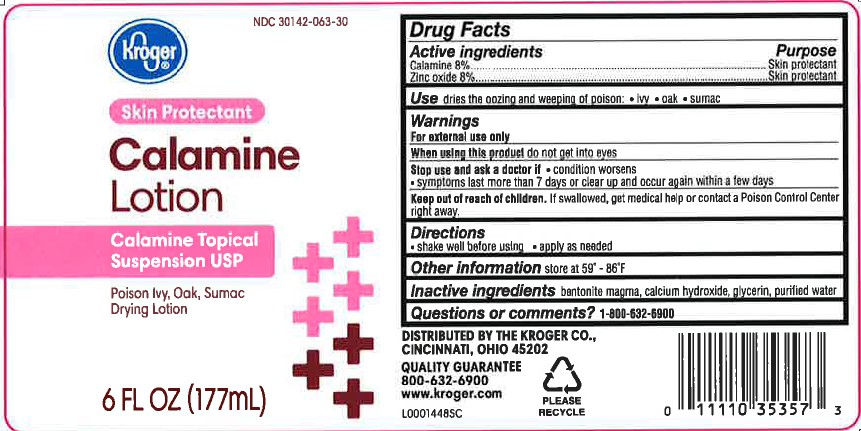 DRUG LABEL: Calamine
NDC: 30142-063 | Form: LOTION
Manufacturer: The Kroger Co.
Category: otc | Type: HUMAN OTC DRUG LABEL
Date: 20260227

ACTIVE INGREDIENTS: FERRIC OXIDE RED 8 g/1 mL; ZINC OXIDE 8 g/1 mL
INACTIVE INGREDIENTS: BENTONITE; CALCIUM HYDROXIDE; GLYCERIN; WATER

Kroger 063.001/063AA
Calamine Lotion

Active ingredients

Calamine 8%
Zinc oxide 8%

Purpose

Skin Protectant

Use

dries the oozing and weeping of poison:

- ivy
- oak
- sumac

Warnings

For external use only

When using this product

do not get into eyes

Stop use and ask a doctor if

- condition worsens
- symptoms last more than 7 days or clear up and occur again within a few days

Keep out of reach of children.

If swallowed, get medical help or contact a Poison Control Center right away.

Directions

- shake well before using
- apply as needed

Other information

store at 59⁰ - 86⁰ F

Inactive ingredients

bentonite magma, calcium hydroxide, glycerin, purified water

Questions or comments?

1-800-632-6900

adverse reactions

DISTRIBUTED BY THE KROGER CO

CINCINNATI, OHIO 45202

QUALITY GUARANTEE

www.kroger.com

PLEASE RECYCLE

principal display panel

NDC 30142-063-30

Kroger®

SKIN PROTECTANT

Calamine

Lotion

Suspension USP

Poison Ivy, Oak and Sumac Drying Lotion

6 FL OZ (177 mL)